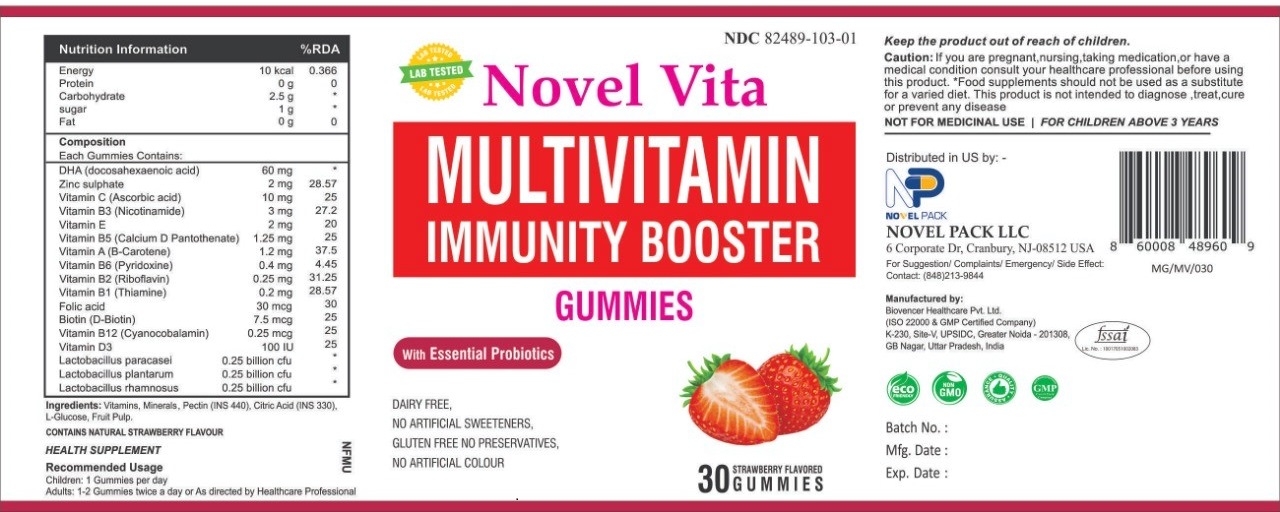 DRUG LABEL: NOVEL VITA
NDC: 82489-103 | Form: GUM, CHEWING
Manufacturer: NOVEL PACK LLC
Category: other | Type: DIETARY SUPPLEMENT
Date: 20220504

ACTIVE INGREDIENTS: ASCORBIC ACID 10 mg/1 1; NIACIN 3 mg/1 1; TOCOPHEROL 2 mg/1 1; PANTOTHENIC ACID 1.25 mg/1 1; BETA CAROTENE 1.2 mg/1 1; PYRIDOXINE 0.4 mg/1 1; RIBOFLAVIN 0.25 mg/1 1; THIAMINE 0.2 mg/1 1; FOLIC ACID 0.03 mg/1 1; BIOTIN 0.0075 mg/1 1; CYANOCOBALAMIN 0.000255 mg/1 1; CHOLECALCIFEROL 0.0025 mg/1 1
INACTIVE INGREDIENTS: ANHYDROUS CITRIC ACID; PECTIN; DEXTROSE

NOVEL VITA
MULTIVITAMIN
IMMUNITY BOOSTER

STATEMENT OF IDENTITY

NOVEL VITA

MULTIVITAMIN

IMMUNITY BOOSTER

GUMMIES

Storage Condition

Store at a temperature not exceeding 25 °C in dry place

Recommended Usage

Children: 1 Gummies per day

Adults: 1-2 Gummies twice a day or As directed by Healthcare Professional

Caution

Keep the product out of reach of children.

If you are pregnant, nursing, taking medication, or have a medical condition consult your healthcare professional before using this product. "Food supplements should not be used as a substitute for a varied diet. The product is not intended to diagnose, treat, cure or prevent any disease.

NOT FOR MEDICINAL USE

FOR CHILDREN ABOVE 3 YEARS